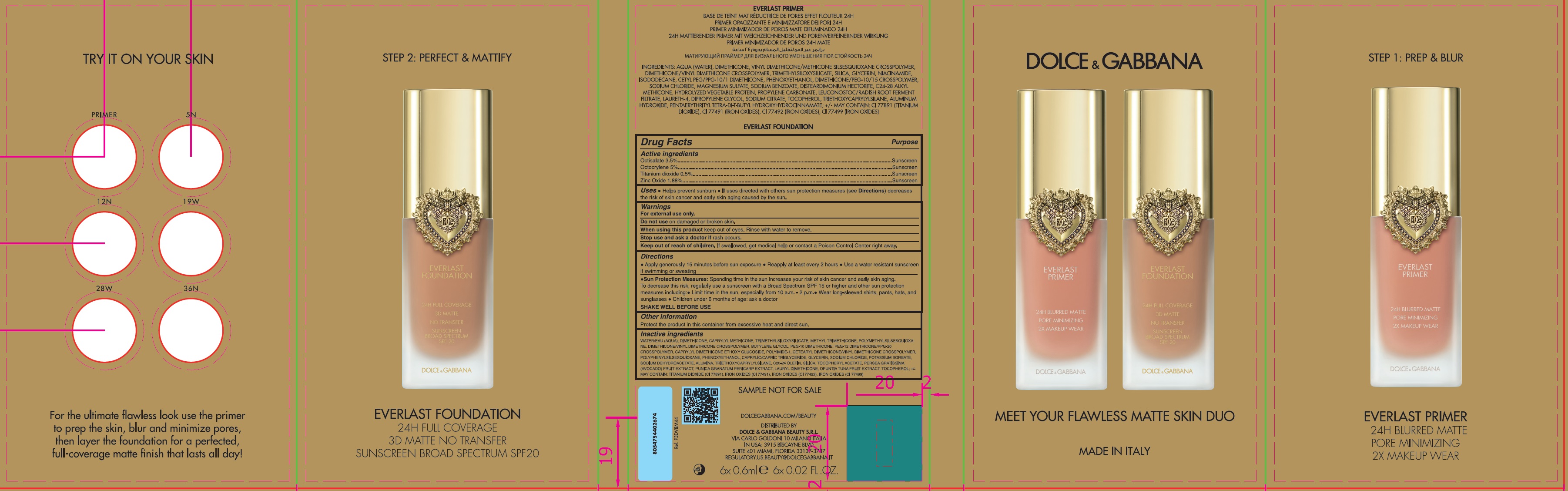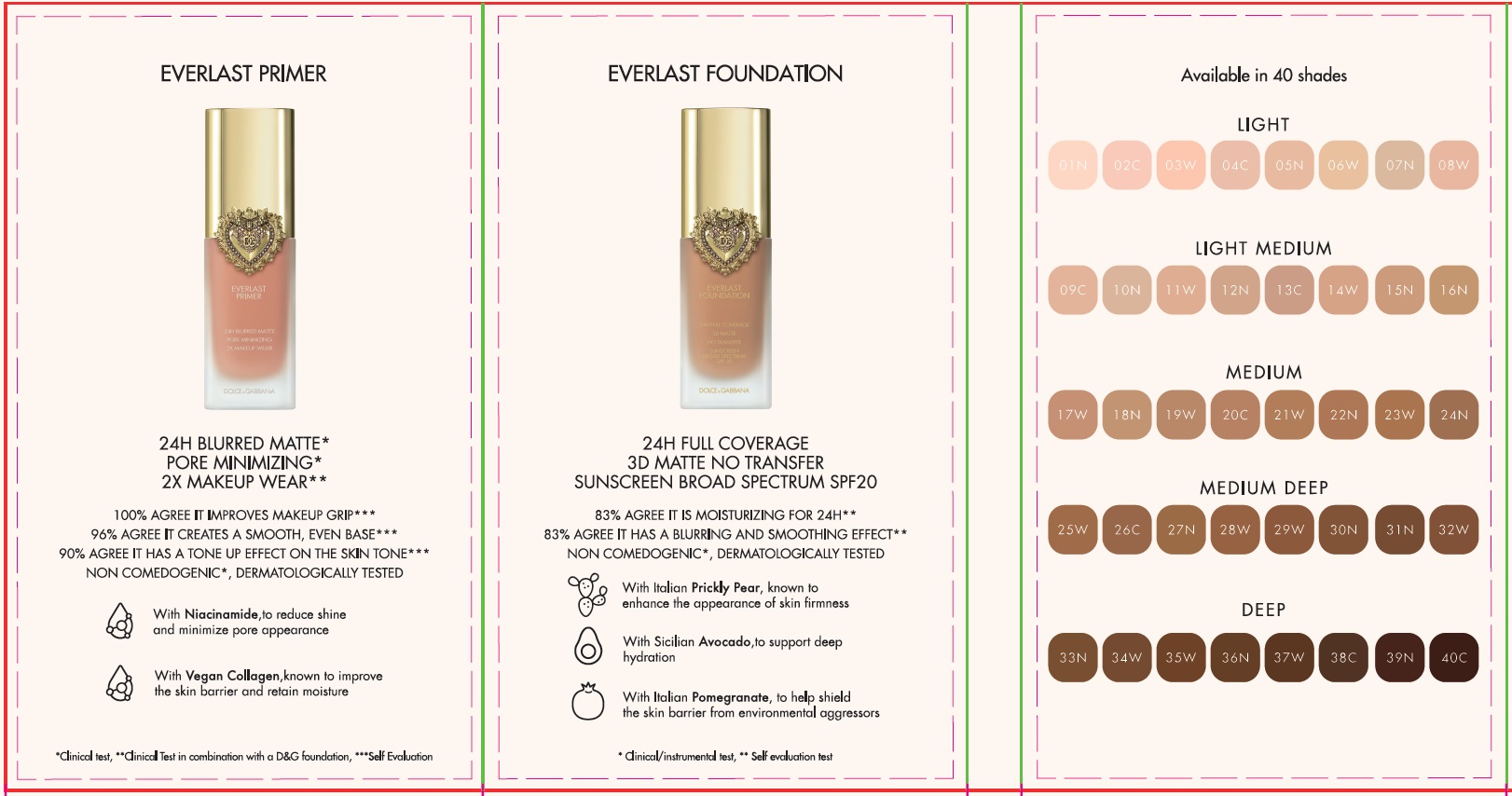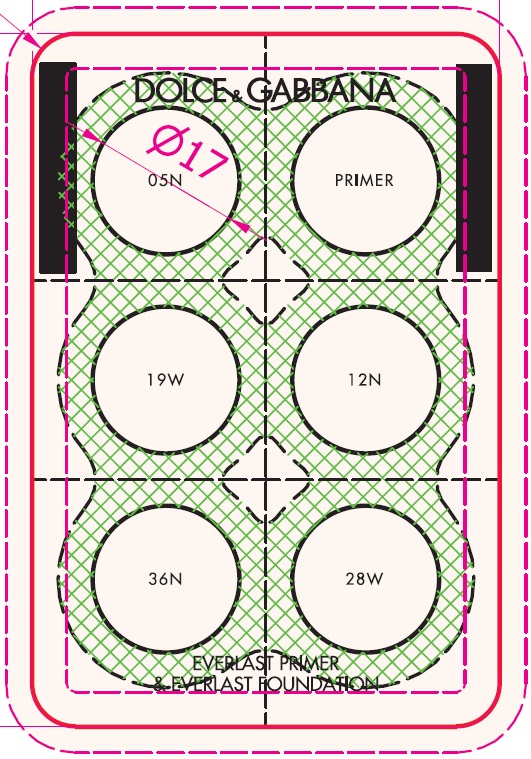 DRUG LABEL: DOLCE and GABBANA MEET YOUR FLAWLESS MATTE SKIN DUO - EVERLAST PRIMER EVERLAST FOUNDATION
NDC: 84003-041 | Form: KIT | Route: TOPICAL
Manufacturer: DOLCE & GABBANA BEAUTY SRL
Category: otc | Type: HUMAN OTC DRUG LABEL
Date: 20250903

ACTIVE INGREDIENTS: OCTISALATE 35 mg/1 mL; OCTOCRYLENE 50 mg/1 mL; TITANIUM DIOXIDE 5 mg/1 mL; ZINC OXIDE 18.8 mg/1 mL; OCTISALATE 35 mg/1 mL; OCTOCRYLENE 50 mg/1 mL; TITANIUM DIOXIDE 5 mg/1 mL; ZINC OXIDE 18.8 mg/1 mL; OCTISALATE 35 mg/1 mL; OCTOCRYLENE 50 mg/1 mL; TITANIUM DIOXIDE 5 mg/1 mL; ZINC OXIDE 18.8 mg/1 mL; OCTISALATE 35 mg/1 mL; OCTOCRYLENE 50 mg/1 mL; TITANIUM DIOXIDE 5 mg/1 mL; ZINC OXIDE 18.8 mg/1 mL; OCTISALATE 35 mg/1 mL; OCTOCRYLENE 50 mg/1 mL; TITANIUM DIOXIDE 5 mg/1 mL; ZINC OXIDE 18.8 mg/1 mL
INACTIVE INGREDIENTS: TOCOPHEROL; WATER; DIMETHICONE; CAPRYLYL TRISILOXANE; METHYL TRIMETHICONE; POLYMETHYLSILSESQUIOXANE (4.5 MICRONS); BUTYLENE GLYCOL; PEG-12 DIMETHICONE/PPG-20 CROSSPOLYMER; CAPRYLYL DIMETHICONE ETHOXY GLUCOSIDE; PHENOXYETHANOL; MEDIUM-CHAIN TRIGLYCERIDES; GLYCERIN; SODIUM CHLORIDE; POTASSIUM SORBATE; SODIUM DEHYDROACETATE; ALUMINUM OXIDE; TRIETHOXYCAPRYLYLSILANE; SILICON DIOXIDE; .ALPHA.-TOCOPHEROL ACETATE; AVOCADO; POMEGRANATE FRUIT RIND; OPUNTIA TUNA FRUIT; TOCOPHEROL; WATER; DIMETHICONE; CAPRYLYL TRISILOXANE; METHYL TRIMETHICONE; POLYMETHYLSILSESQUIOXANE (4.5 MICRONS); BUTYLENE GLYCOL; PEG-12 DIMETHICONE/PPG-20 CROSSPOLYMER; CAPRYLYL DIMETHICONE ETHOXY GLUCOSIDE; PHENOXYETHANOL; MEDIUM-CHAIN TRIGLYCERIDES; GLYCERIN; SODIUM CHLORIDE; POTASSIUM SORBATE; SODIUM DEHYDROACETATE; ALUMINUM OXIDE; TRIETHOXYCAPRYLYLSILANE; SILICON DIOXIDE; .ALPHA.-TOCOPHEROL ACETATE; AVOCADO; POMEGRANATE FRUIT RIND; OPUNTIA TUNA FRUIT; TOCOPHEROL; WATER; DIMETHICONE; CAPRYLYL TRISILOXANE; METHYL TRIMETHICONE; POLYMETHYLSILSESQUIOXANE (4.5 MICRONS); BUTYLENE GLYCOL; PEG-12 DIMETHICONE/PPG-20 CROSSPOLYMER; CAPRYLYL DIMETHICONE ETHOXY GLUCOSIDE; PHENOXYETHANOL; MEDIUM-CHAIN TRIGLYCERIDES; GLYCERIN; SODIUM CHLORIDE; POTASSIUM SORBATE; SODIUM DEHYDROACETATE; ALUMINUM OXIDE; TRIETHOXYCAPRYLYLSILANE; SILICON DIOXIDE; .ALPHA.-TOCOPHEROL ACETATE; AVOCADO; POMEGRANATE FRUIT RIND; OPUNTIA TUNA FRUIT; TOCOPHEROL; WATER; DIMETHICONE; CAPRYLYL TRISILOXANE; BUTYLENE GLYCOL; PEG-12 DIMETHICONE/PPG-20 CROSSPOLYMER; CAPRYLYL DIMETHICONE ETHOXY GLUCOSIDE; PHENOXYETHANOL; MEDIUM-CHAIN TRIGLYCERIDES; GLYCERIN; SODIUM CHLORIDE; POTASSIUM SORBATE; SODIUM DEHYDROACETATE; ALUMINUM OXIDE; TRIETHOXYCAPRYLYLSILANE; SILICON DIOXIDE; .ALPHA.-TOCOPHEROL ACETATE; AVOCADO; POMEGRANATE FRUIT RIND; OPUNTIA TUNA FRUIT; METHYL TRIMETHICONE; POLYMETHYLSILSESQUIOXANE (4.5 MICRONS); TOCOPHEROL; WATER; DIMETHICONE; CAPRYLYL TRISILOXANE; METHYL TRIMETHICONE; POLYMETHYLSILSESQUIOXANE (4.5 MICRONS); BUTYLENE GLYCOL; PEG-12 DIMETHICONE/PPG-20 CROSSPOLYMER; CAPRYLYL DIMETHICONE ETHOXY GLUCOSIDE; PHENOXYETHANOL; MEDIUM-CHAIN TRIGLYCERIDES; GLYCERIN; SODIUM CHLORIDE; POTASSIUM SORBATE; SODIUM DEHYDROACETATE; ALUMINUM OXIDE; TRIETHOXYCAPRYLYLSILANE; SILICON DIOXIDE; .ALPHA.-TOCOPHEROL ACETATE; AVOCADO; POMEGRANATE FRUIT RIND; OPUNTIA TUNA FRUIT

DOLCE & GABBANA MEET YOUR FLAWLESS MATTE SKIN DUO - EVERLAST PRIMER - EVERLAST FOUNDATION

Active ingredients

Octisalate 3.5%

Octocrylene 5%

Titanium dioxide 0.5%

Zinc Oxide 1.88%

Purpose

Sunscreen

Uses

- Helps prevent sunburn
- If uses directed with others sun protection measures (see Directions) decreases the risk of skin cancer and early skin aging caused by the sun.

Warnings

For external use only.

Do not use

on damaged or broken skin.

When using this product

keep out of eyes. Rinse with water to remove.

Stop use and ask a doctor if

rash occurs.

Keep out of reach of children.

If swallowed, get medical help or contact a Poison Control Center right away.

Directions

- Apply generously 15 minutes before sun exposure
- Reapply at least every 2 hours
- Use a water resistant sunscreen if swimming or sweating
- Sun Protection Measures:Spending time in the sun increases your risk of skin cancer and early skin aging. To decrease this risk, regularly use a sunscreen with a Broad Spectrum SPF 15 or higher and other sun protection measures including:
- Limit time in the sun, especially from 10 a.m.- 2 p.m.
- wear long-sleeved shirts, pants, hats, and sunglasses
- Children under 6 months of age: ask a doctor

SHAKE WELL BEFORE USE

Other information

Protect the product in this container from excessive heat and direct sun.

Inactive ingredients

WATER/EAU (AQUA), DIMETHICONE, CAPRYLYL METHICONE, TRIMETHYLSILOXYSILICATE, METHYL TRIMETHICONE, POLYMETHYLSILSESQUIOXANE, DIMETHICONE/VINYL DIMETHICONE CROSSPOLYMER, BUTYLENE GLYCOL, PEG-10 DIMETHICONE, PEG-12 DIMETHICONE/PPG-20 CROSSPOLYMER, CAPRYLYL DIMETHICONE ETHOXY GLUCOSIDE, POLYIMIDE-1, CETEARYL DIMETHICONE/VINYL DIMETHICONE CROSSPOLYMER, POLYPHENYLSILSESQUIOXANE, PHENOXYETHANOL, CAPRYLIC/CAPRIC TRIGLYCERIDE, GLYCERIN, SODIUM CHLORIDE, POTASSIUM SORBATE, SODIUM DEHYDROACETATE, ALUMINA, TRIETHOXYCAPRYLSILANE, C20-24 OLEFIN, SILICA, TOCOPHERYL ACETATE, PERSEA GRATISSIMA (AVOCADO) FRUIT EXTRACT, PUNICA GRANATUM PERICARP EXTRACT, LAURYL DIMETHICONE, OPUNTIA TUNA FRUOT EXTRACT, TOCOPHEROL; +/- MAY CONTAIN: TITANIUM DIOXIDE (CI 77891), IRON OXIDES (CI 77491), IRON OXIDES (CI 77492), IRON OXIDES (CI 77499)